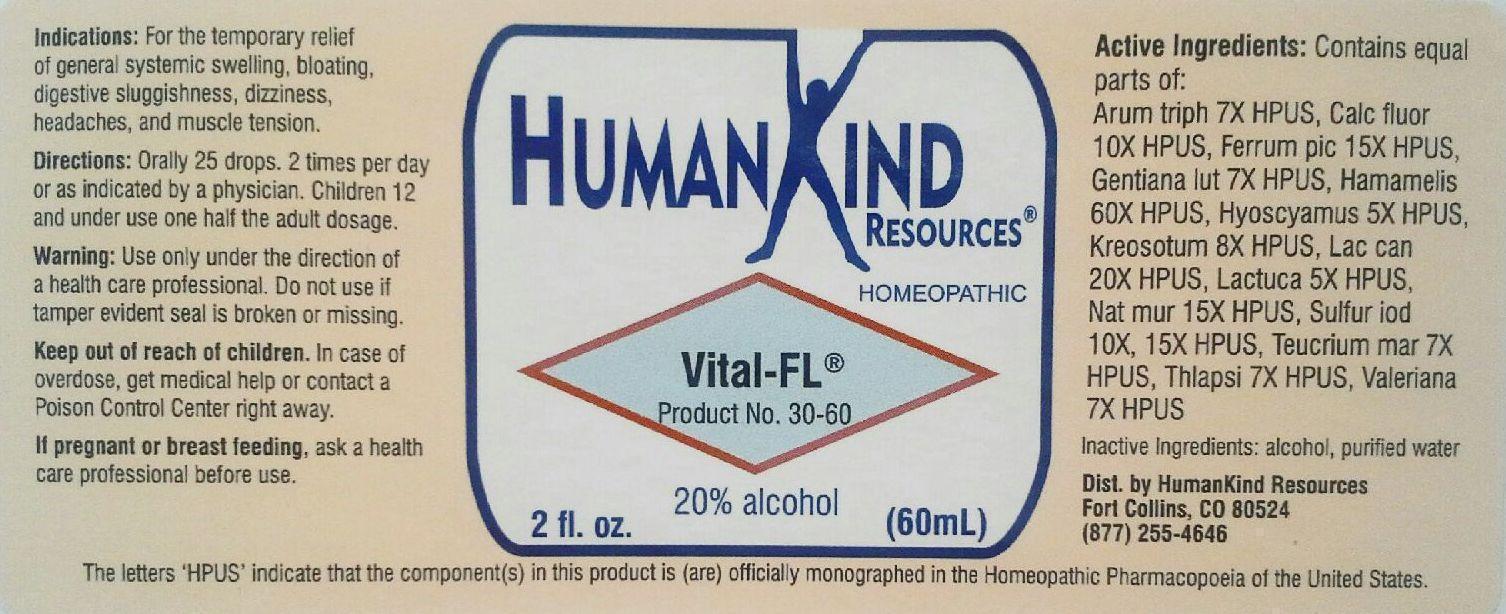 DRUG LABEL: Vital-FL
NDC: 64616-108 | Form: LIQUID
Manufacturer: Vitaltiy Works, Inc.
Category: homeopathic | Type: HUMAN OTC DRUG LABEL
Date: 20251217

ACTIVE INGREDIENTS: ARISAEMA TRIPHYLLUM ROOT 7 [hp_X]/1 mL; CALCIUM FLUORIDE 10 [hp_X]/1 mL; FERRIC PICRATE 15 [hp_X]/1 mL; GENTIANA LUTEA ROOT 7 [hp_X]/1 mL; HAMAMELIS VIRGINIANA ROOT BARK/STEM BARK 60 [hp_X]/1 mL; HYOSCYAMUS NIGER 5 [hp_X]/1 mL; WOOD CREOSOTE 8 [hp_X]/1 mL; CANIS LUPUS FAMILIARIS MILK 20 [hp_X]/1 mL; LACTUCA VIROSA 5 [hp_X]/1 mL; SODIUM CHLORIDE 15 [hp_X]/1 mL; SULFUR IODIDE 15 [hp_X]/1 mL; TEUCRIUM MARUM 7 [hp_X]/1 mL; CAPSELLA BURSA-PASTORIS 7 [hp_X]/1 mL; VALERIAN 7 [hp_X]/1 mL
INACTIVE INGREDIENTS: ALCOHOL; WATER

Vital-FL

Vital-FL

Arum Triphyllum 7X Lac Caninum 20X

Calcarea Fluorica 10X Lactuca Virosa 5X

Ferrum Picricum 15X Natrum Muriaticum 15X

Gentiana Lutea 7X Sulphur Iodatum 10X, 15X

Hamamelis Virginiana 60X Teucrium Marum 7X

Hyoscynamus Niger 5X Thlaspi Bursa Pastoris 7X

Kreosotum 8X Valeriana Officinalis 7X

Vital-FL

Alcohol, Purified Water

Vital-FL

Use only under the direction of a health care professional. Do not use if tamper evident seal is broken or missing.

Vital-FL

Keep out of reach of children. In case of overdose, get medical help or contat a Poison Control Center right away.

Vital-FL

For the temporary relief of general systemic, swelling, bloating, digestive sluggishness, dizziness, headaches, and muscle tension.

Vital-FL

Orally 25 drops, 2 times per day or as indicated by physician. Children 12 and under use one half the adult dosage.

Vital-FL

Assits the body in establishing and maintaining a natural balance and flow of body fluids.